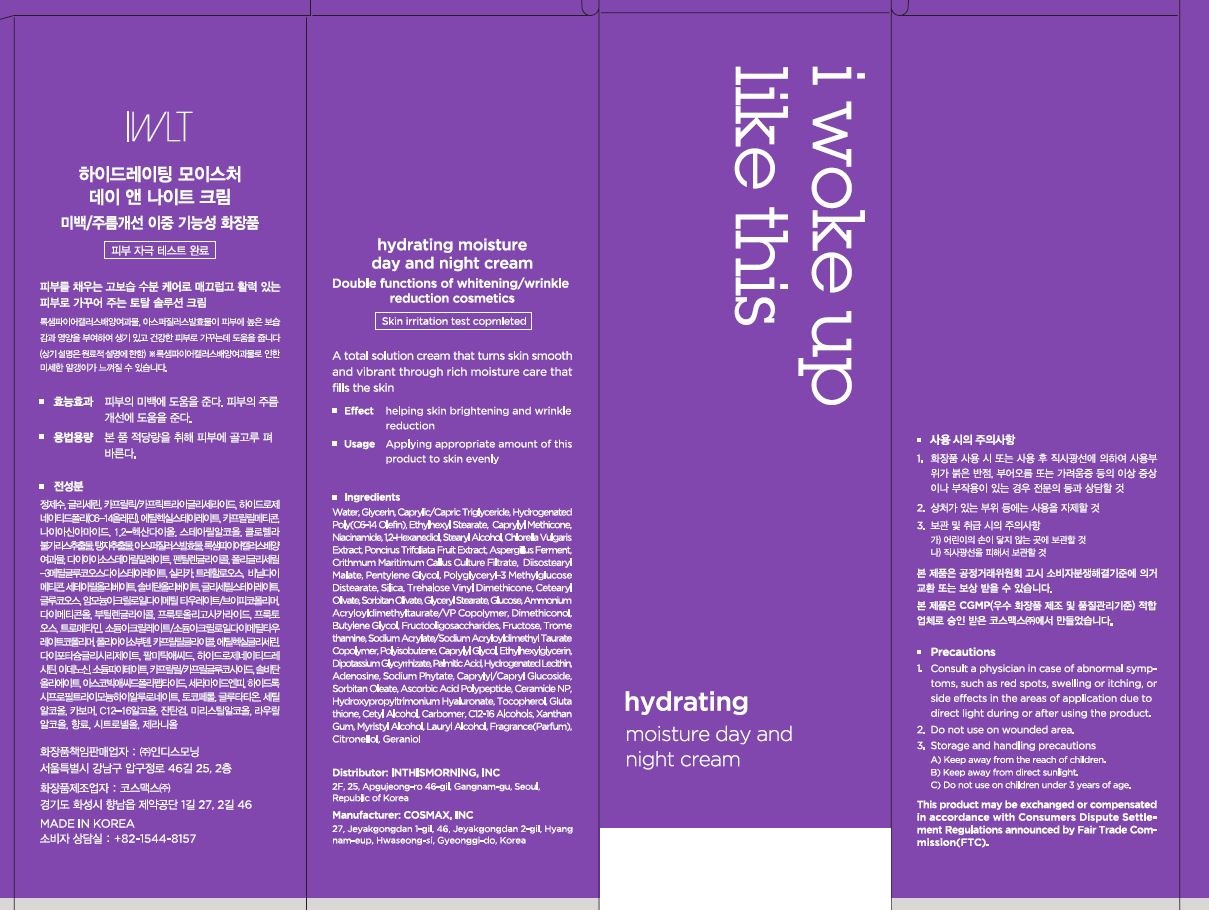 DRUG LABEL: Hydrating moisture day and nightcream
NDC: 71217-0071 | Form: CREAM
Manufacturer: inthismorning co ltd
Category: otc | Type: HUMAN OTC DRUG LABEL
Date: 20230613

ACTIVE INGREDIENTS: .BETA.-CITRONELLOL, (R)- 0.0090402 g/100 mL; GERANIOL 0.003019275 g/100 mL
INACTIVE INGREDIENTS: WATER; GLYCERIN

Drug Facts

ACTIVE INGREDIENT

citronellol, geraniol

INACTIVE INGREDIENT

water, glycerin, etc

PURPOSE

moisturizing, whitening, wrinkle care

keep out or reach of the children

INDICATIONS AND USAGE

apply proper amount to the skin

WARNINGS

This product is for exeternal use only. Do not use for internal use
Storage and handling precautions
If possible, avoid direct sunlight and store in cool and area of low humidity in order to maintain the quality of the product and avoid misuse
Avoid placing the product near fire and store out in reach of children

- consult a physician in case of abnormal symptoms, such as red spots, swelling or itching, or side effects in the areas of application due to direct light during or after using the product

- do not use on wounded area

DOSAGE AND ADMINISTRATION

for external use only